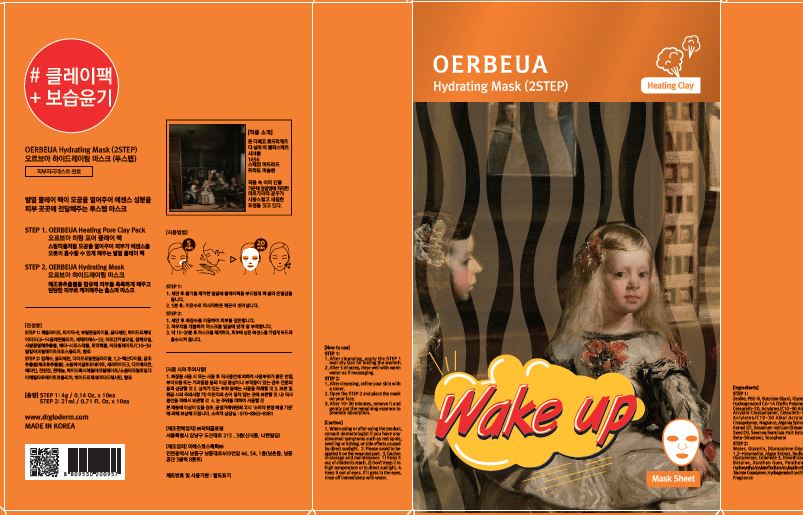 DRUG LABEL: OERBEUA HYDRATING MASK
NDC: 71342-0026 | Form: LIQUID
Manufacturer: DR.GLODERM
Category: otc | Type: HUMAN OTC DRUG LABEL
Date: 20180109

ACTIVE INGREDIENTS: GLYCERIN 4.975 g/100 mL
INACTIVE INGREDIENTS: WATER; PANTHENOL

Drug Facts

ACTIVE INGREDIENT

Glycerin

INACTIVE INGREDIENT

Water, panthenol, etc

PURPOSE

Skin Protectant

keep out of reach of the children

INDICATIONS AND USAGE

step 1:

after cleansing, apply the STEP 1 over dry facr for feeling the warmth

after 5 minutes, rinse well with warm water as if massaging

step 2:

after cleansing refine your skin with a toner

oper the STEP 2 and place the maks on your face

after 10~20 minutes, remove it and gently pat the remaining essence to promote absorption

WARNINGS

1. If the following symptoms occur after product use, stop using the product immediately and consult a dermatologist (continuous use can exacerbate the symptoms).
1) Occurrence of red spots, swelling, itchiness, and other skin irritation
2) If the symptoms above occur after the application area is exposed to direct sunlight
2. Do not use on open wounds, eczema, and other skin irritations
3. Precaution for Storage and Handling
1) Close the lid after use
2) Keep out of reach of infants and children
3) Do not to store in a place with high/low temperature and exposed to direct sunlight

DOSAGE AND ADMINISTRATION

for external use only